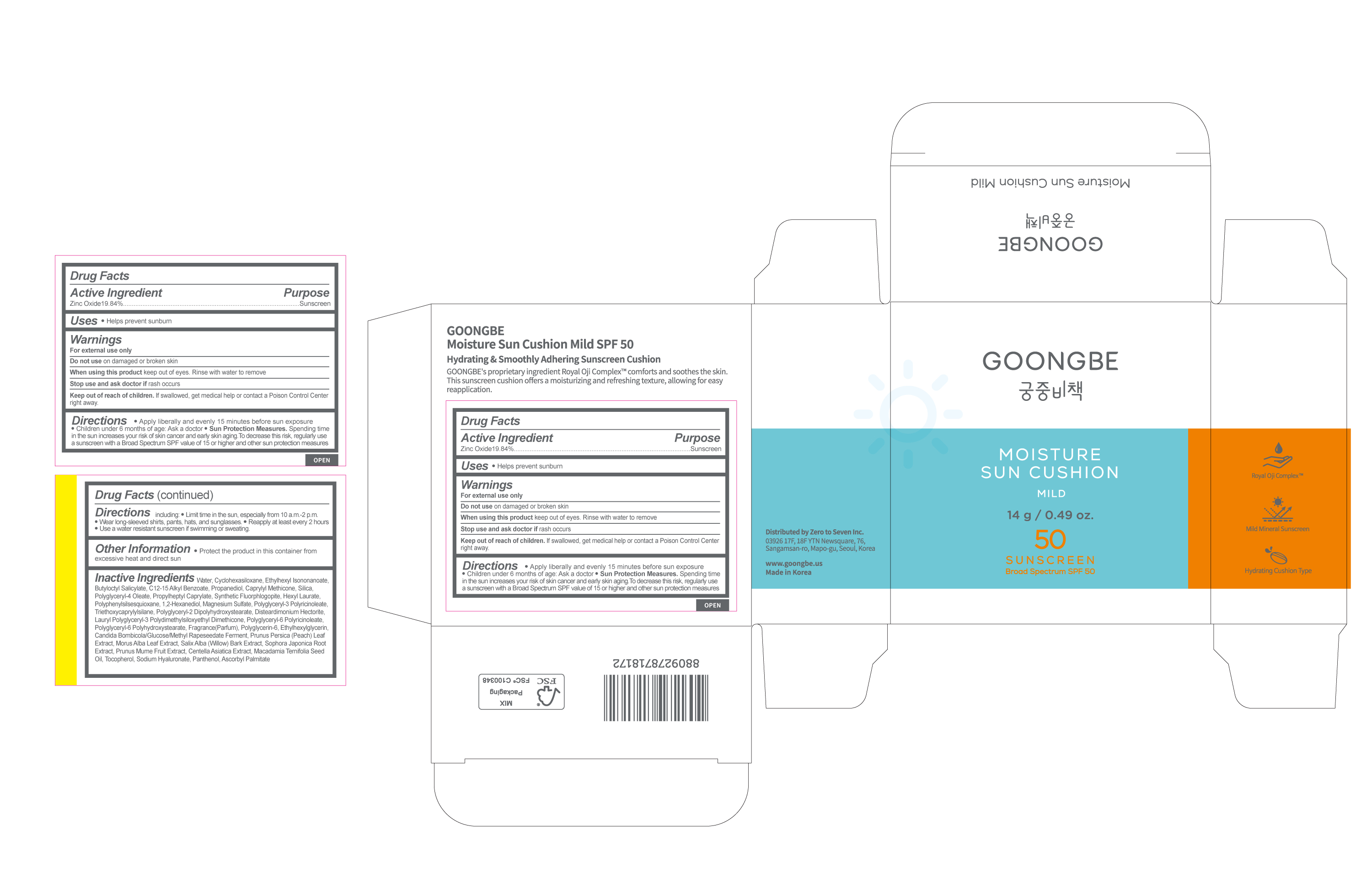 DRUG LABEL: GOONGBE Moisture Sun Cushion Mild SPF 50
NDC: 43319-074 | Form: LOTION
Manufacturer: Zero to Seven Inc.
Category: otc | Type: HUMAN OTC DRUG LABEL
Date: 20241118

ACTIVE INGREDIENTS: ZINC OXIDE 19.84 g/100 g
INACTIVE INGREDIENTS: ETHYLHEXYL ISONONANOATE; BUTYLOCTYL SALICYLATE; PROPANEDIOL; WATER

Dosage & Administration

Dosage form: Lotion

Administration: Topical

Warnings

For external use only

Do not use on damaged or broken skin.

When using this product keep out of eyes.

Rinse with water to remove Stop use and ask doctor if rash occurs

Keep out of reach of children. If swallowed, get medical help or contact a Poison Control Center right away

Inactive Ingredients

Water, Cyclohexasiloxane, Ethylhexyl Isononanoate, Butyloctyl Salicylate, C12-15 Alkyl Benzoate, Propanediol, Caprylyl Methicone, Silica, Polyglyceryl-4 Oleate, Propylheptyl Caprylate, Synthetic Fluorphlogopite, Hexyl Laurate, Polyphenylsilsesquioxane, 1,2-Hexanediol, Magnesium Sulfate, Polyglyceryl-3 Polyricinoleate, Triethoxycaprylylsilane, Polyglyceryl-2 Dipolyhydroxystearate, Disteardimonium Hectorite, Lauryl Polyglyceryl-3 Polydimethylsiloxyethyl Dimethicone, Polyglyceryl-6 Polyricinoleate, Polyglyceryl-6 Polyhydroxystearate, Fragrance(Parfum), Polyglycerin-6, Ethylhexylglycerin, Candida Bombicola/Glucose/Methyl Rapeseedate Ferment, Prunus Persica (Peach) Leaf Extract, Morus Alba Leaf Extract, Salix Alba (Willow) Bark Extract, Sophora Japonica Root Extract, Prunus Mume Fruit Extract, Centella Asiatica Extract, Macadamia Ternifolia Seed Oil, Tocopherol, Sodium Hyaluronate, Panthenol, Ascorbyl Palmitate

Usage

Helps prevent sunburn

Keep out of reach of children.

If swallowed, get medical help or contact a Poison Control Center right away.

Purpose

sunscreen